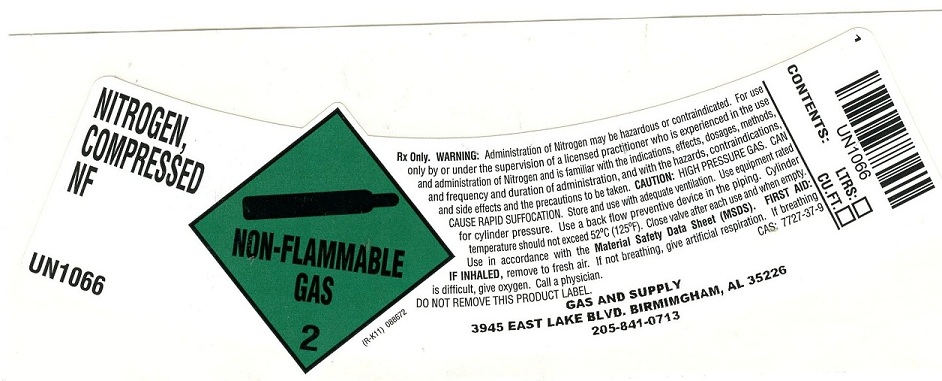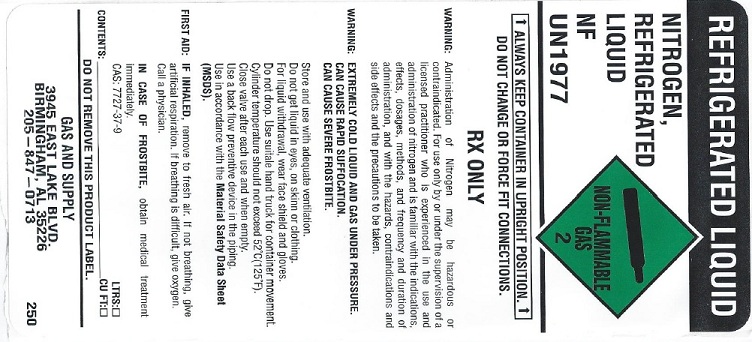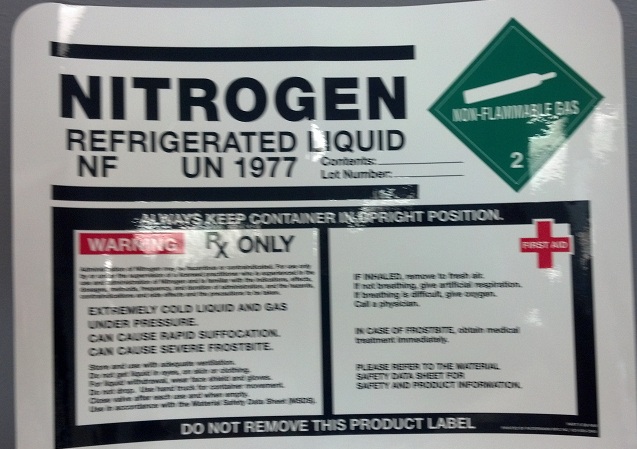 DRUG LABEL: Nitrogen
NDC: 53991-002 | Form: GAS
Manufacturer: SOUTHERN GAS AND SUPPLY, INC.
Category: prescription | Type: HUMAN PRESCRIPTION DRUG LABEL
Date: 20251208

ACTIVE INGREDIENTS: NITROGEN 995 mL/1 L

Nitrogen

PACKAGE LABEL

NITROGEN, COMPRESSED NF UN1066

NON-FLAMMABLE GAS 2

Rx ONLY. WARNING: Administration of Nitrogen may be hazardous or contraindicated. For use only by or under the supervision of a licensed practitioner who is experienced in the use and administration of Nitrogen and is familiar with the indications, effects, dosage, methods, and frequency and duration of administration, and with the hazards, contraindications, and side effects and the precautions to be taken. CAUTION: HIGH PRESSURE GAS. CAN CAUSE RAPID SUFFOCATION. Store and use with adequate ventilation. Use equipment rated for cylinder pressure. Use a back flow preventive device in the piping. Cylinder temperature should not exceed 52 degrees C (125 degrees F). Close valve after each use and when empty. Use in accordance with the Material Safety Data Sheet (MSDS). FIRST AID: IF INHALED, remove to fresh air. If not breathing, give artificial respiration. If breathing is difficulty, give oxygen. Call a physician. CAS: 7727-37-9

DO NOT REMOVE THIS PRODUCT LABEL.

GAS AND SUPPLY

3945 EAST LAKE BLVD. BIRMINGHAM, AL 35226

205-841-0713

UN1066

CONTENTS: LTRS. CU.FT.

PACKAGE LABEL

REFRIGERATED LIQUID

NITROGEN, REFRIGERATED LIQUID NF UN1977

ALWAYS KEEP CONTAINER IN UPRIGHT POSITION

DO NOT CHANGE OR FORCE FIT CONNECTIONS.

RX ONLY

WARNING: Administration of Nitrogen may be hazardous or contraindicated. For use only by or under the supervision of a licensed practitioner who is experienced in the use and administration of nitrogen and is familiar with the indications, effects, dosages, methods, and frequency and duration of administration, and with the hazards, contraindications and side effects and the precautions to be taken.

WARNING: EXTREMELY COLD LIQUID AND GAS UNDER PRESSURE. CAN CAUSE RAPID SUFFOCATION. CAN CAUSE SEVERE FROSTBITE.

Store and use with adequate ventilation. Do not get liquid in eyes, on skin or clothing. For liquid withdrawal, wear face shield and gloves. Do not drop. Use suitable hand truck for container movement. Cylinder temperature should not exceed 52 degrees C (125 degrees F). Close valve after each use and when empty. Use a back flow preventive device in the piping. Use in accordance with the Material Safety Data Sheet (MSDS).

FIRST AID: IF INHALED, remove to fresh air. If not breathing, give artificial respiration. If breathing is difficult, give oxygen. Call a physician. IN CASE OF FROSTBITE, obtain medical treatment immediately. CAS: 7727-37-9

CONTENTS: LTRS CU FT

DO NOT REMOVE THIS PRODUCT LABEL.

GAS AND SUPPLY

3945 EAST LAKE BLVD.

BIRMINGHAM, AL 35226

205-847-0713

PACKAGE LABEL

NITROGEN REFRIGERATED LIQUID NF UN1977

Contents: Lot Number: NON-FLAMMABLE 2

ALWAYS KEEP CONTAINER IN UPRIGHT POSITION.

WARNING RX ONLY

Administration of Nitrogen may be hazardous or contraindicated. for use only by or under the supervision of a licensed practitioner who is experienced in the use and administration of Nitrogen and is familiar with the indications, effects, dosages, methods, frequency, and duration of administration, and the hazards, contraindications and side effects and the precautions to be taken.

EXTREMELY COLD LIQUID AND GAS UNDER PRESSURE. CAN CAUSE RAPID SUFFOCATION. CAN CAUSE SEVERE FROSTBITE. Store and use with adequate ventilation. Do not get liquid in eyes, on skin or clothing. For liquid withdrawal, wear face shield and gloves. Do not drop. Use hand truck for container movement. Clove valve after each use and when empty. Use in accordance with the Material Safety Data Sheet (MSDS).

IN INHALED, remove to fresh air. If not breathing, give artificial respiration. If breathing is difficult, give oxygen. Call a physician. IN CASE OF FROSTBITE, obtain medical treatment immediately.

PLEASE REFER TO THE MATERIAL SAFETY DATA SHEET FOR SAFETY AND PRODUCT INFORMATION.